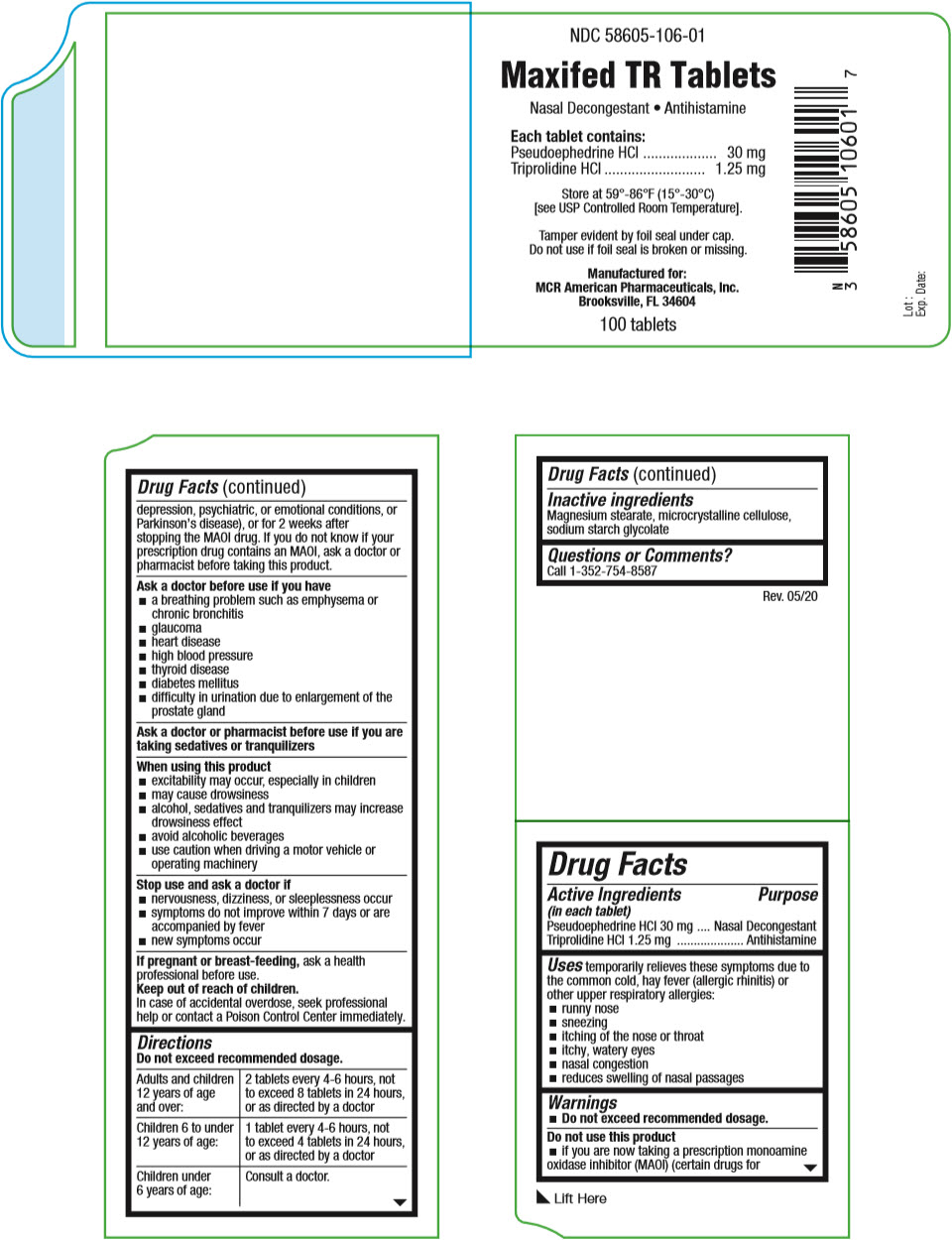 DRUG LABEL: Maxifed TR
NDC: 58605-106 | Form: TABLET
Manufacturer: MCR American Pharmaceuticals, Inc.
Category: otc | Type: HUMAN OTC DRUG LABEL
Date: 20200623

ACTIVE INGREDIENTS: Pseudoephedrine Hydrochloride 30 mg/1 1; Triprolidine Hydrochloride 1.25 mg/1 1
INACTIVE INGREDIENTS: Magnesium Stearate; Microcrystalline Cellulose; SODIUM STARCH GLYCOLATE TYPE A POTATO

Maxifed TR Tablets

Drug Facts

ACTIVE INGREDIENT

Active Ingredients (in each tablet) | Purpose
Pseudoephedrine HCl 30 mg | Nasal Decongestant
Triprolidine HCl 1.25 mg | Antihistamine

Uses

temporarily relieves these symptoms due to the common cold, hay fever (allergic rhinitis) or other upper respiratory allergies:

- runny nose
- sneezing
- itching of the nose or throat
- itchy, watery eyes
- nasal congestion
- reduces swelling of nasal passages

Warnings

- Do not exceed recommended dosage.

Do not use this product

- if you are now taking a prescription monoamine oxidase inhibitor (MAOI) (certain drugs for depression, psychiatric, or emotional conditions, or Parkinson's disease), or for 2 weeks after stopping the MAOI drug. If you do not know if your prescription drug contains an MAOI, ask a doctor or pharmacist before taking this product.

Ask a doctor before use if you have

- a breathing problem such as emphysema or chronic bronchitis
- glaucoma
- heart disease
- high blood pressure
- thyroid disease
- diabetes mellitus
- difficulty in urination due to enlargement of the prostate gland

Ask a doctor or pharmacist before use if you are taking sedatives or tranquilizers

When using this product

- excitability may occur, especially in children
- may cause drowsiness
- alcohol, sedatives and tranquilizers may increase drowsiness effect
- avoid alcoholic beverages
- use caution when driving a motor vehicle or operating machinery

Stop use and ask a doctor if

- nervousness, dizziness, or sleeplessness occur
- symptoms do not improve within 7 days or are accompanied by fever
- new symptoms occur

PREGNANCY OR BREAST FEEDING

If pregnant or breast-feeding, ask a health professional before use.

Keep out of reach of children.

In case of accidental overdose, seek professional help or contact a Poison Control Center immediately.

Directions

Do not exceed recommended dosage.

Adults and children 12 years of age and over: | 2 tablets every 4-6 hours, not to exceed 8 tablets in 24 hours, or as directed by a doctor
Children 6 to under 12 years of age: | 1 tablet every 4-6 hours, not to exceed 4 tablets in 24 hours, or as directed by a doctor
Children under 6 years of age: | Consult a doctor.

Inactive ingredients

Magnesium stearate, microcrystalline cellulose, sodium starch glycolate

Questions or Comments?

Call 1-352-754-8587

PRINCIPAL DISPLAY PANEL - 100 Tablet Bottle Label

NDC 58605-106-01

Maxifed TR Tablets

Nasal Decongestant • Antihistamine

Each tablet contains:

Pseudoephedrine HCl
30 mg
Triprolidine HCl
1.25 mg

Store at 59°-86°F (15°-30°C)
[see USP Controlled Room Temperature].

Tamper evident by foil seal under cap.
Do not use if foil seal is broken or missing.

Manufactured for:
MCR American Pharmaceuticals, Inc.
Brooksville, FL 34604

100 tablets